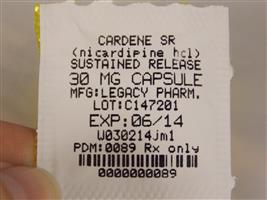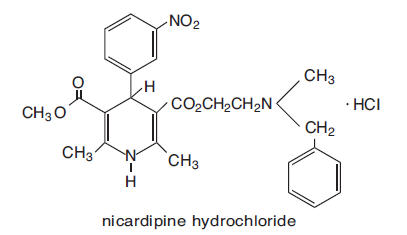 DRUG LABEL: Cardene
                                    
NDC: 68151-0089 | Form: CAPSULE, EXTENDED RELEASE
Manufacturer: Carilion Materials Management
Category: prescription | Type: HUMAN PRESCRIPTION DRUG LABEL
Date: 20160806

ACTIVE INGREDIENTS: NICARDIPINE HYDROCHLORIDE 30 mg/1 1
INACTIVE INGREDIENTS: STARCH, CORN; MAGNESIUM STEARATE; CELLULOSE, MICROCRYSTALLINE; CORN; LACTOSE; METHACRYLIC ACID - ETHYL ACRYLATE COPOLYMER (1:1) TYPE A

CARDENE SR (nicardipine hydrochloride) SUSTAINED RELEASE CAPSULES®

DESCRIPTION

CARDENE SR is a sustained release formulation of CARDENE . CARDENE SR capsules for oral administration each contain 30 mg, 45 mg or 60 mg of nicardipine hydrochloride. Nicardipine hydrochloride is a calcium ion influx inhibitor (slow channel blocker or calcium entry blocker).®®

Nicardipine hydrochloride is a dihydropyridine derivative with the IUPAC (International Union of Pure and Applied Chemistry) chemical name (±)-2-(benzyl-methyl amino) ethyl methyl 1,4-dihydro-2,6 dimethyl-4-(m-nitrophenyl)-3, 5-pyridinedicarboxylate monohydrochloride, and it has the following structure:

Nicardipine hydrochloride is a greenish-yellow, odorless, crystalline powder that melts at about 169°C. It is freely soluble in chloroform, methanol and glacial acetic acid, sparingly soluble in anhydrous ethanol, slightly soluble in n-butanol, water, 0.01 M potassium dihydrogen phosphate, acetone and dioxane, very slightly soluble in ethyl acetate, and practically insoluble in benzene, ether and hexane. It has a molecular weight of 515.99.

CARDENE SR is available in hard gelatin capsules containing 30 mg, 45 mg or 60 mg nicardipine hydrochloride. All strengths contain a two component capsule fill. A powder component containing 25% of total nicardipine hydrochloride dose contains pregelatinized starch and magnesium stearate as inactive ingredients. A spherical granule component containing 75% of total nicardipine hydrochloride dose also contains microcrystalline cellulose, starch, lactose and methacrylic acid copolymer Type C as inactive ingredients.

The colorants used in the 30-mg capsules are titanium dioxide, FD&C Red No. 40 and red iron oxide, and the colorants used in the 45-mg and 60-mg capsule are titanium dioxide and FD&C Blue No. 2.

CLINICAL PHARMACOLOGY

Mechanism of Action

Nicardipine is a calcium entry blocker (slow channel blocker or calcium ion antagonist) that inhibits the transmembrane influx of calcium ions into cardiac muscle and smooth muscle without changing serum calcium concentrations. The contractile processes of cardiac muscle and vascular smooth muscle are dependent upon the movement of extracellular calcium ions into these cells through specific ion channels. The effects of nicardipine are more selective to vascular smooth muscle than cardiac muscle. In animal models, nicardipine produces relaxation of coronary vascular smooth muscle at drug levels that cause little or no negative inotropic effect.

Pharmacokinetics and Metabolism

Nicardipine is completely absorbed following oral doses administered as capsules, and the systemic bioavailability is about 35% following a 30-mg oral dose at steady-state. The pharmacokinetics of nicardipine are nonlinear due to saturable hepatic first-pass metabolism.

Following oral administration of CARDENE SR, plasma levels are detectable as early as 20 minutes and maximal plasma levels are achieved as a broad peak generally between 1 and 4 hours. The average terminal plasma half-life of nicardipine is 8.6 hours. Following oral administration increasing doses result in disproportionate increases in plasma levels. Steady-state C values following 30-, 45- and 60-mg doses every 12 hours averaged 13.4, 34.0, and 58.4 ng/mL, respectively. Hence, increasing the dose twofold increases maximum plasma levels 4-fold to 5-fold. A similar disproportionate increase is observed with AUC. In comparison with equivalent daily doses of CARDENE capsules, CARDENE SR shows a significant reduction in C . CARDENE SR also has somewhat lower bioavailability than CARDENE except at the highest dose. Minimum plasma levels produced by equivalent daily doses are similar. CARDENE SR thus exhibits significantly reduced fluctuation in plasma levels in comparison to CARDENE capsules.maxmax

When CARDENE SR was administered with a high-fat breakfast, mean C was 45% lower, AUC was 25% lower and trough levels were 75% higher than when CARDENE SR was given in the fasting state. Thus, taking CARDENE SR with the meal reduced the fluctuation in plasma levels. Clinical trials establishing the safety and efficacy of CARDENE SR were carried out in patients without regard to the timing of meals.max

Nicardipine is highly protein bound (>95%) in human plasma over a wide concentration range.

Nicardipine is metabolized extensively by the liver; less than 1% of intact drug is detected in the urine. Following a radioactive oral dose in solution, 60% of the radioactivity was recovered in the urine and 35% in feces. Most of the dose (over 90%) was recovered within 48 hours of dosing. Nicardipine does not induce its own metabolism and does not induce hepatic microsomal enzymes.

Nicardipine plasma levels following administration of CARDENE SR in hypertensive patients with moderate renal impairment (creatinine clearance 10 to 55 mL/min) were significantly higher following a single-oral dose and at steady-state than in hypertensive patients with mildly impaired renal function (creatinine clearance >55 mL/min). After 45-mg CARDENE SR bid at steady-state, C and AUC were 2-fold to 3-fold higher in the patients with moderate renal impairment. Plasma levels in patients with mildly impaired renal function were similar to those in normal subjects.max

In patients with severe renal impairment undergoing routine hemodialysis, plasma levels following a single dose of CARDENE SR were not significantly different from those patients with mildly impaired renal function.

Because nicardipine is extensively metabolized by the liver, the plasma levels of the drug are influenced by changes in hepatic function. Following administration of CARDENE capsules, nicardipine plasma levels were higher in patients with severe liver disease (hepatic cirrhosis confirmed by liver biopsy or presence of endoscopically-confirmed esophageal varices) than in normal subjects. After 20-mg CARDENE bid at steady-state, C and AUC were 1.8-fold and 4-fold higher, and the terminal half-life was prolonged to 19 hours in these patients. CARDENE SR has not been studied in patients with severe liver disease.max

Geriatric Pharmacokinetics

The pharmacokinetics of CARDENE SR in elderly hypertensive subjects (mean age 70 years) were compared to those in younger hypertensive subjects (mean age 44 years). After a single dose and after 1 week of dosing with CARDENE SR there were no significant differences in C , T , AUC or clearance between the young and elderly subjects. In both groups of subjects, steady-state plasma levels were significantly higher than following a single dose. In the elderly subjects, a disproportional increase in plasma levels with dose was observed similar to that observed in normal subjects.maxmax

Hemodynamics

In man, nicardipine produces a significant decrease in systemic vascular resistance. The degree of vasodilation and the resultant hypotensive effects are more prominent in hypertensive patients. In hypertensive patients, nicardipine reduces the blood pressure at rest and during isometric and dynamic exercise. In normotensive patients, a small decrease of about 9 mm Hg in systolic and 7 mm Hg in diastolic blood pressure may accompany this fall in peripheral resistance. An increase in heart rate may occur in response to the vasodilation and decrease in blood pressure, and in a few patients this heart rate increase may be pronounced. In clinical studies mean heart rate at time of peak plasma levels was usually increased by 5 to 10 beats per minute compared to placebo, with the greater increases at higher doses, while there was no difference from placebo at the end of the dosing interval. Hemodynamic studies following intravenous dosing in patients with coronary artery disease and normal or moderately abnormal left ventricular function have shown significant increases in ejection fraction and cardiac output with no significant change, or a small decrease, in left ventricular end-diastolic pressure (LVEDP). Although there is evidence that nicardipine increases coronary blood flow, there is no evidence that this property plays any role in its effectiveness in stable angina. In patients with coronary artery disease, intracoronary administration of nicardipine caused no direct myocardial depression. CARDENE does, however, have a negative inotropic effect in some patients with severe left ventricular dysfunction and could, in patients with very impaired function, lead to worsened failure.

“Coronary Steal,” the detrimental redistribution of coronary blood flow in patients with coronary artery disease (diversion of blood from under-perfused areas toward better perfused areas), has not been observed during nicardipine treatment. On the contrary, nicardipine has been shown to improve systolic shortening in normal and hypokinetic segments of myocardial muscle, and radionuclide angiography has confirmed that wall motion remained improved during an increase in oxygen demand. Nonetheless, occasional patients have developed increased angina upon receiving nicardipine. Whether this represents steal in those patients, or is the result of increased heart rate and decreased diastolic pressure, is not clear.

In patients with coronary artery disease nicardipine improves L.V. diastolic distensibility during the early filling phase, probably due to a faster rate of myocardial relaxation in previously under-perfused areas. There is little or no effect on normal myocardium, suggesting the improvement is mainly by indirect mechanisms such as afterload reduction and reduced ischemia. Nicardipine has no negative effect on myocardial relaxation at therapeutic doses. The clinical consequences of these properties are as yet undemonstrated.

Electrophysiologic Effects

In general, no detrimental effects on the cardiac conduction system were seen with the use of CARDENE.

Nicardipine increased the heart rate when given intravenously during acute electrophysiologic studies and prolonged the corrected QT interval to a minor degree. The sinus node recovery times and SA conduction times were not affected by the drug. The PA, AH and HV intervals* and the functional and effective refractory periods of the atrium were not prolonged by nicardipine and the relative and effective refractory periods of the His-Purkinje system were slightly shortened after intravenous nicardipine.

Renal Function

There is a transient increase in electrolyte excretion, including sodium. CARDENE does not cause generalized fluid retention, as measured by weight changes.

*PA=conduction time from high to low right atrium, AH=conduction time from low right atrium to His bundle deflection or AV nodal conduction time, HV=conduction time through the His bundle and the bundle branch-Purkinje system.

Effects in Hypertension

CARDENE SR produced decreases in both systolic and diastolic blood pressure throughout the dosing interval in clinical trials. The antihypertensive efficacy of CARDENE SR administered twice daily has been demonstrated using in-clinic blood pressure measures in placebo-controlled trials involving patients with mild to moderate hypertension and in trials using 12 or 24 hour ambulatory blood pressure monitoring.

INDICATIONS AND USAGE

CARDENE SR is indicated for the treatment of hypertension. CARDENE SR may be used alone or in combination with other anti-hypertensive drugs.

CONTRAINDICATIONS

CARDENE is contraindicated in patients with hypersensitivity to the drug.

Because part of the effect of CARDENE is secondary to reduced afterload, the drug is also contraindicated in patients with advanced aortic stenosis. Reduction of diastolic pressure by any means in these patients may worsen rather than improve myocardial oxygen balance.

WARNINGS

Increased Angina in Patients With Angina

In short-term, placebo-controlled angina trials with CARDENE (an immediate release oral dosage form of nicardipine), about 7% of patients on CARDENE (compared with 4% of patients on placebo) have developed increased frequency, duration or severity of angina. Comparisons with beta-blockers also show a greater frequency of increased angina, 4% vs 1%. The mechanism of this effect has not been established.

Use in Patients With Congestive Heart Failure

Although preliminary hemodynamic studies in patients with congestive heart failure have shown that CARDENE reduced afterload without impairing myocardial contractility, it has a negative inotropic effect in vitro and in some patients. Caution should be exercised when using the drug in congestive heart failure patients, particularly in combination with a beta-blocker.

Beta-Blocker Withdrawal

CARDENE is not a beta-blocker and therefore gives no protection against the dangers of abrupt beta-blocker withdrawal; any such withdrawal should be by gradual reduction of the dose of beta-blocker, preferably over 8 to 10 days.

PRECAUTIONS

General

Because CARDENE decreases peripheral resistance, careful monitoring of blood pressure during the initial administration and titration of CARDENE is suggested. CARDENE, like other calcium channel blockers, may occasionally produce symptomatic hypotension. Caution is advised to avoid systemic hypotension when administering the drug to patients who have sustained an acute cerebral infarction or hemorrhage. Blood Pressure:

Since the liver is the major site of biotransformation and since CARDENE is subject to first-pass metabolism, CARDENE should be used with caution in patients having impaired liver function or reduced hepatic blood flow. Patients with severe liver disease developed elevated blood levels (fourfold increase in AUC) and prolonged half-life (19 hours) of CARDENE. Use in Patients With Impaired Hepatic Function:

When 45-mg CARDENE SR bid was given to hypertensive patients with moderate renal impairment, mean AUC and C values were approximately 2-fold to 3-fold higher than in patients with mild renal impairment. Doses in these patients must be adjusted. Mean AUC and C values were similar in patients with mildly impaired renal function and normal volunteers (see and). Use in Patients With Impaired Renal Function:maxmax CLINICAL PHARMACOLOGYDOSAGE AND ADMINISTRATION

Drug Interactions

In controlled clinical studies, adrenergic beta-receptor blockers have been frequently administered concomitantly with CARDENE. The combination is well tolerated. Beta-Blockers:

Cimetidine increases CARDENE plasma levels. Patients receiving the two drugs concomitantly should be carefully monitored. Cimetidine:

Some calcium blockers may increase the concentration of digitalis preparations in the blood. CARDENE usually does not alter the plasma levels of digoxin; however, serum digoxin levels should be evaluated after concomitant therapy with CARDENE is initiated. Digoxin:

Severe hypotension has been reported during fentanyl anesthesia with concomitant use of a beta-blocker and a calcium channel blocker. Even though such interactions were not seen during clinical studies with CARDENE, an increased volume of circulating fluids might be required if such an interaction were to occur. Fentanyl Anesthesia:

Concomitant administration of nicardipine and cyclosporine results in elevated plasma cyclosporine levels. Plasma concentrations of cyclosporine should therefore be closely monitored, and its dosage reduced accordingly, in patients treated with nicardipine. Cyclosporine:

When therapeutic concentrations of furosemide, propranolol, dipyridamole, warfarin, quinidine or naproxen were added to human plasma (in vitro), the plasma protein binding of CARDENE was not altered.

Carcinogenesis, Mutagenesis, Impairment of Fertility

Rats treated with nicardipine in the diet (at concentrations calculated to provide daily dosage levels of 5, 15 or 45 mg/kg/day) for 2 years showed a dose-dependent increase in thyroid hyperplasia and neoplasia (follicular adenoma/carcinoma). One- and 3-month studies in the rat have suggested that these results are linked to a nicardipine-induced reduction in plasma thyroxine (T4) levels with a consequent increase in plasma levels of thyroid stimulating hormone (TSH). Chronic elevation of TSH is known to cause hyperstimulation of the thyroid. In rats on an iodine deficient diet, nicardipine administration for 1 month was associated with thyroid hyperplasia that was prevented by T4 supplementation. Mice treated with nicardipine in the diet (at concentrations calculated to provide daily dosage levels of up to 100 mg/kg/day) for up to 18 months showed no evidence of neoplasia of any tissue and no evidence of thyroid changes. There was no evidence of thyroid pathology in dogs treated with up to 25 mg nicardipine/kg/day for 1 year and no evidence of effects of nicardipine on thyroid function (plasma T4 and TSH) in man.

There was no evidence of a mutagenic potential of nicardipine in a battery of genotoxicity tests conducted on microbial indicator organisms, in micronucleus tests in mice and hamsters, or in a sister chromatid exchange study in hamsters.

No impairment of fertility was seen in male or female rats administered nicardipine at oral doses as high as 100 mg/kg/day (50 times the maximum recommended daily dose in man, assuming a patient weight of 60 kg).

Pregnancy

Pregnancy Category C. Nicardipine was embryocidal when administered orally to pregnant Japanese White rabbits, during organogenesis, at 150 mg/kg/day (a dose associated with marked body weight gain suppression in the treated doe) but not at 50 mg/kg/day (25 times the maximum recommended dose in man). No adverse effects on the fetus were observed when New Zealand albino rabbits were treated, during organogenesis, with up to 100 mg nicardipine/kg/day (a dose associated with significant mortality in the treated doe). In pregnant rats administered nicardipine orally at up to 100 mg/kg/day (50 times the maximum recommended human dose) there was no evidence of embryolethality or teratogenicity. However, dystocia, reduced birth weights, reduced neonatal survival and reduced neonatal weight gain were noted. There are no adequate and well-controlled studies in pregnant women. CARDENE SR should be used during pregnancy only if the potential benefit justifies the potential risk to the fetus.

Nursing Mothers

Studies in rats have shown significant concentrations of nicardipine in maternal milk following oral administration. For this reason it is recommended that women who wish to breastfeed should not take this drug.

Pediatric Use

Safety and effectiveness in pediatric patients have not been established.

Geriatric use

Pharmacokinetic parameters did not differ significantly between elderly hypertensive subjects (mean age: 70 years) and younger hypertensive subjects (mean age: 44 years) after 1 week of treatment with CARDENE SR (see). CLINICAL PHARMACOLOGY: Geriatric Pharmacokinetics

Clinical studies of nicardipine did not include sufficient numbers of subjects aged 65 and over to determine whether they respond differently from younger subjects. Other reported clinical experience has not identified differences in responses between the elderly and younger patients. In general, dose selection for an elderly patient should be cautious, usually starting at the low end of the dosing range, reflecting the greater frequency of decreased hepatic, renal, or cardiac function, and of concomitant disease or other drug therapy.

ADVERSE REACTIONS

In multiple-dose US and foreign controlled studies, 667 patients received CARDENE SR. In these studies adverse events were elicited by non-directed and in some cases directed questioning; adverse events were generally not serious and about 9% of patients withdrew prematurely from the studies because of them.

Hypertension

The incidence rates of adverse events in hypertensive patients were derived from placebo-controlled clinical trials. Following are the rates of adverse events for CARDENE SR (n=322) and placebo (n=140), respectively, that occurred in 0.6% of patients or more on CARDENE SR. These represent events considered probably drug related by the investigator. Where the frequency of adverse events for CARDENE SR and placebo is similar, causal relationship is uncertain. The only dose-related effect was pedal edema.

Percentage of Patients With Probably Drug Related Adverse Events in Placebo-Controlled Studies

Adverse Event | CARDENE SR (n=322) | Placebo (n=140)
Headache | 6.2 | 7.1
Pedal Edema | 5.9 | 1.4
Vasodilatation | 4.7 | 1.4
Palpitation | 2.8 | 1.4
Nausea | 1.9 | 0.7
Dizziness | 1.6 | 0.7
Asthenia | 0.9 | 0.7
Postural Hypotension | 0.9 | 0
Increased UrinaryFrequency | 0.6 | 0
Pain | 0.6 | 0
Rash | 0.6 | 0
Sweating Increased | 0.6 | 0
Vomiting | 0.6 | 0

Incidence (%) of Discontinuations Due to Any Adverse Event in Placebo-Controlled Studies

Adverse Event | CARDENE SR (n=322) | Placebo (n=140)
Headache | 2.5 | 1.4
Palpitation | 2.2 | 0.7
Dizziness | 1.9 | 0.7
Asthenia | 1.9 | 0
Pedal Edema | 1.2 | 0
Nausea | 1.2 | 0
Rash | 0.9 | 0.7
Diarrhea | 0.9 | 0
Tachycardia | 0.9 | 0
Blurred Vision | 0.6 | 0
Chest Pain | 0.6 | 0
Face Edema | 0.6 | 0
Myocardial Infarct | 0.6 | 0
Vasodilatation | 0.6 | 0
Vomiting | 0.6 | 0

Uncontrolled experience in over 300 patients with hypertension treated for up to 27.5 months with CARDENE SR has shown no unexpected adverse events or increase in incidence of adverse events compared to the controlled clinical trials.

Rare Events

The following rare adverse events have been reported in clinical trials or the literature:

infection, allergic reaction Body as a Whole:

hypotension, atypical chest pain, peripheral vascular disorder, ventricular extrasystoles, ventricular tachycardia, angina pectoris Cardiovascular:

sore throat, abnormal liver chemistries Digestive:

arthralgia Musculoskeletal:

hot flashes, vertigo, hyperkinesia, impotence, depression, confusion, anxiety Nervous:

rhinitis, sinusitis Respiratory:

tinnitus, abnormal vision, blurred vision Special Senses:

Angina

Data are available from only 91 patients with chronic stable angina pectoris who received CARDENE SR 30 to 60 mg administered twice daily in open-label clinical trials. Fifty-eight of these patients were treated for at least 30 days. The four most frequently reported adverse events thought by the investigators to be probably related to the use of CARDENE SR were vasodilatation (5.5%), pedal edema (4.4%), asthenia (4.4%), and dizziness (3.3%).

OVERDOSAGE

Three overdosages with CARDENE or CARDENE SR have been reported. Two occurred in adults, 1 of whom ingested 600 mg of CARDENE and the other 2160 mg of CARDENE SR. Symptoms included marked hypotension, bradycardia, palpitations, flushing, drowsiness, confusion, and slurred speech. All symptoms resolved without sequelae. The third over-dosage occurred in a 1-year-old child who ingested half of the powder in a 30-mg CARDENE capsule. The child remained asymptomatic.

Based on results obtained in laboratory animals, overdosage may cause systemic hypotension, bradycardia (following initial tachycardia) and progressive atrioventricular conduction block. Reversible hepatic function abnormalities and sporadic focal hepatic necrosis were noted in some animal species receiving very large doses of nicardipine.

standard measures (for example, evacuation of gastric contents, elevation of extremities, attention to circulating fluid volume, and urine output) including monitoring of cardiac and respiratory functions should be implemented. The patient should be positioned so as to avoid cerebral anoxia. Frequent blood pressure determinations are essential. Vasopressors are clinically indicated for patients exhibiting profound hypotension. Intravenous calcium gluconate may help reverse the effects of calcium entry blockade. For treatment of overdose

DOSAGE AND ADMINISTRATION

The dose of CARDENE SR should be individually adjusted according to the blood pressure response beginning with 30 mg two times daily. The effective doses in clinical trials have ranged from 30 mg to 60 mg two times daily. The maximum blood pressure lowering effect at steady-state is sustained from 2 hours until 6 hours after dosing.

When initiating therapy or upon increasing dose, blood pressure should be measured 2 to 4 hours after the first dose or dose increase, as well as at the end of a dosing interval.

The total daily dose of immediate release nicardipine (CARDENE) may not be a useful guide to judging the effective dose of CARDENE SR. Patients currently receiving immediate release nicardipine may be titrated with CARDENE SR starting at their current total daily dose of immediate release nicardipine and then reexamined to assess the adequacy of blood pressure control.

Concomitant Use With Other Antihypertensive Agents:

1. : CARDENE may be safely coadministered with thiazide diuretics. Diuretics
2. : CARDENE may be safely coadministered with beta-blockers (see). Beta-Blockers Drug Interactions

Special Patient Populations

Although there is no evidence that CARDENE SR impairs renal function, careful dose titration beginning with 30-mg CARDENE SR bid is advised (see). Renal Insufficiency: PRECAUTIONS

CARDENE SR has not been studied in patients with severe liver impairment (see). Hepatic Insufficiency: PRECAUTIONS

Caution is advised when titrating CARDENE SR dosage in patients with congestive heart failure (see). Congestive Heart Failure: WARNINGS

HOW SUPPLIED

NDC:68151-0089-0 in a PACKAGE of 1 CAPSULE, EXTENDED RELEASES